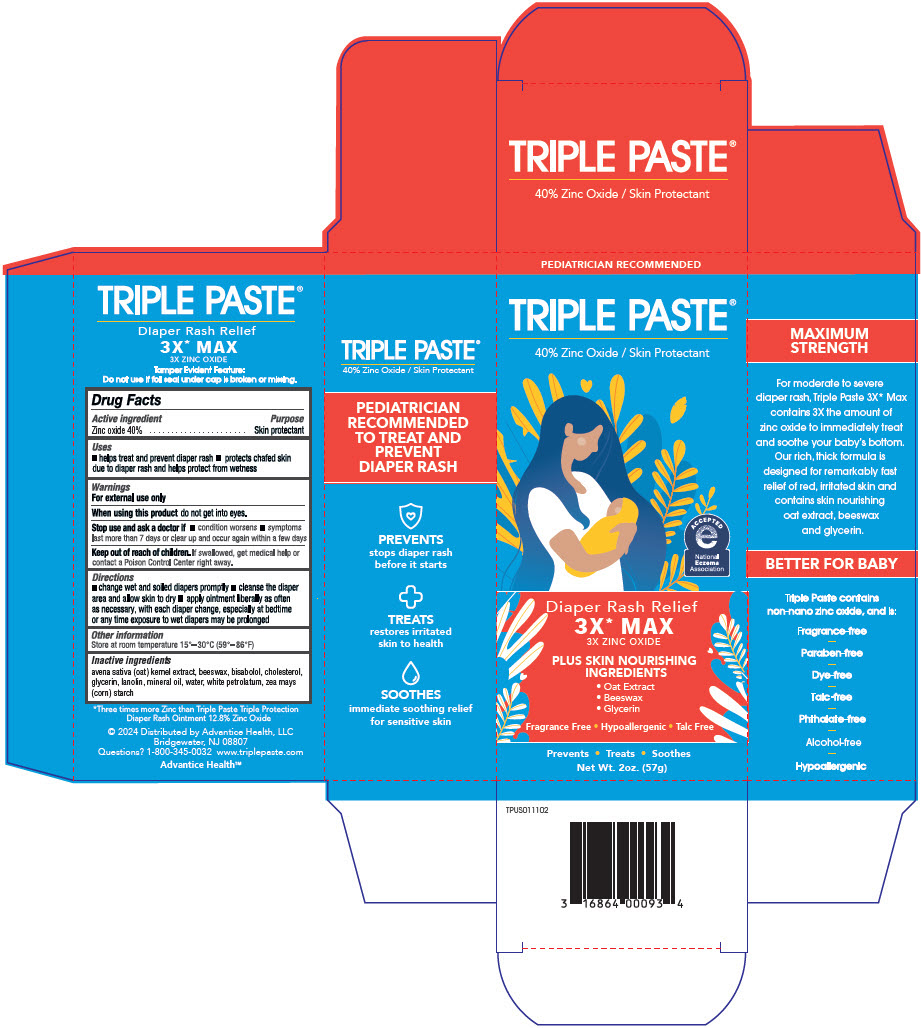 DRUG LABEL: Triple 3x Max Diaper Rash
NDC: 16864-061 | Form: OINTMENT
Manufacturer: Advantice Health, LLC
Category: otc | Type: HUMAN OTC DRUG LABEL
Date: 20251202

ACTIVE INGREDIENTS: ZINC OXIDE 40 g/100 g
INACTIVE INGREDIENTS: BEESWAX; WHITE PETROLATUM; STARCH, CORN; LANOLIN; .ALPHA.-BISABOLOL, (+/-)-; CHOLESTEROL; WATER; GLYCERIN; OAT; MINERAL OIL

Triple Paste 3x Max Diaper Rash Ointment

Drug Facts

Active ingredient

Zinc oxide 40%

Purpose

Skin protectant

Uses

- helps treat and prevent diaper rash
- protects chafed skin due to diaper rash and helps protect from wetness

Warnings

For external use only

When using this productdo not get into eyes.

Stop use and ask a doctor if

- condition worsens
- symptoms last more than 7 days or clear up and occur again within a few days

Keep out of reach of children.If swallowed, get medical help or contact a Poison Control Center right away.

Directions

- change wet and soiled diapers promptly
- cleanse the diaper area and allow skin to dry
- apply ointment liberally as often as necessary, with each diaper change, especially at bedtime or any time exposure to wet diapers may be prolonged

Other information

Store at room temperature 15°-30°C (59°-86°F)

Inactive ingredients

avena sativa (oat) kernel extract, beeswax, bisabolol, cholesterol, glycerin, lanolin, mineral oil, water, white petrolatum, zea mays (corn) starch

Questions?

1-800-345-0032

Distributed by Advantice Health, LLC
Bridgewater, NJ 08807

PRINCIPAL DISPLAY PANEL - 57 g Tube Carton

PEDIATRICIAN RECOMMENDED

TRIPLE PASTE®

40% Zinc Oxide / Skin Protectant

ACCEPTED
e
National
Eczema
Association

Diaper Rash Relief
3X* MAX
3X ZINC OXIDE

PLUS SKIN NOURISHING
INGREDIENTS

- Oat Extract
- Beeswax
- Glycerin

Fragrance Free • Hypoallergenic • Talc Free

Prevents • Treats • Soothes

Net Wt. 2oz. (57g)